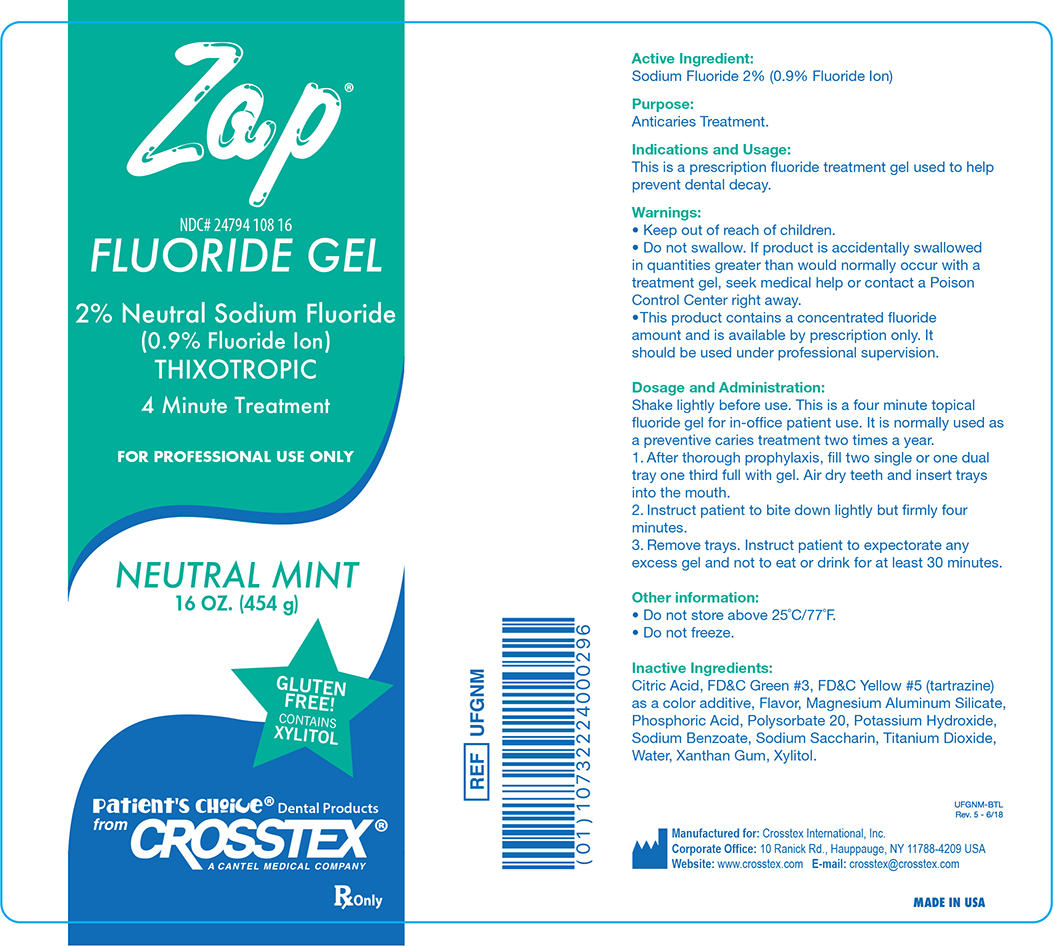 DRUG LABEL: Zap Neutral
NDC: 24794-108 | Form: GEL
Manufacturer: Crosstex International Inc.
Category: prescription | Type: HUMAN PRESCRIPTION DRUG LABEL
Date: 20220119

ACTIVE INGREDIENTS: SODIUM FLUORIDE 4.086 g/454 g
INACTIVE INGREDIENTS: FD&C GREEN NO. 3; FD&C YELLOW NO. 5; CITRIC ACID MONOHYDRATE; MAGNESIUM ALUMINUM SILICATE; PHOSPHORIC ACID; POLYSORBATE 20; SODIUM BENZOATE; SACCHARIN SODIUM; WATER; XANTHAN GUM; XYLITOL; TITANIUM DIOXIDE

Active Ingredient:

Sodium Fluoride 2% (0.9% Fluoride Ion)

Purpose:

Anticaries Treatment.

Indications and Usage:

This is a prescription fluoride treatment gel used to help prevent dental decay.

Warnings:

- Keep out of reach of children.
- Do not swallow. If product is accidentally swallowed in quantities greater than would normally occur with a treatment gel, seek medical help or contact a Poison Control Center right away.
- This product contains a concentrated fluoride amount and is available by prescription only. It should be used under professional supervision.

Dosage and Administration:

Shake lightly before use. This is a four minute topical fluoride gel for in-office patient use. It is normally used as a preventative caries treatment two times a year.

1. After thorough prophylaxsis, fill two single or one dual tray, one third full with gel. Air dry teeth and insert trays into the mouth.

2. Instruct patient to bite down lightly but firmly four minutes.

3. Remove trays. Instruct patient to expectorate any excess gel and not to eat or drink for at least 30 minutes.

Other Information:

- Do not store above 25°C/77°F.
- Do not freeze.

Inactive Ingredients:

Citric Acid, FD&C Green #3, FD&C Yellow #5 (tartrazine) as a color additive, Flavor, Magnesium Aluminum Silicate, Phosphoric Acid, Polysorbate 20, Potassium Hydroxide, Sodium Benzoate, Sodium Saccharin, Titanium Dioxide, Water, Xanthan Gum, Xylitol.